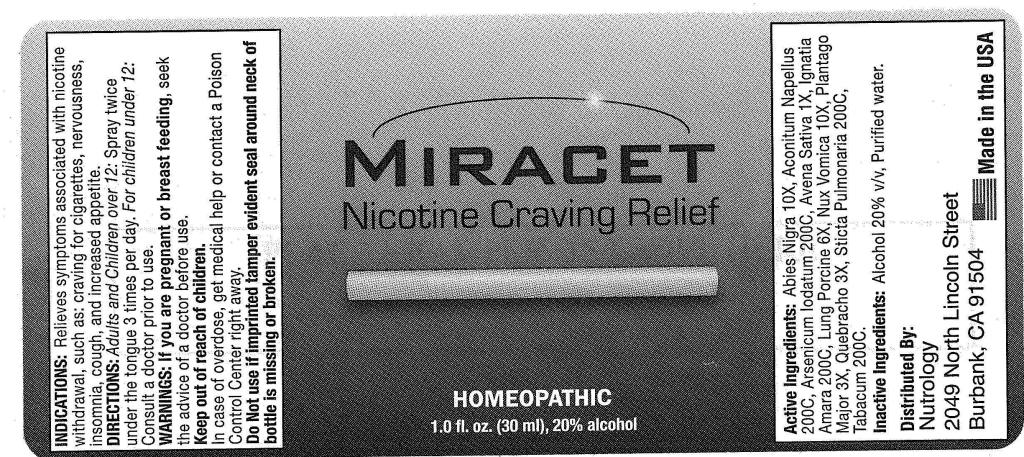 DRUG LABEL: Miracet
NDC: 50845-0134 | Form: SPRAY
Manufacturer: Liddell Laboratories, Inc.
Category: homeopathic | Type: HUMAN OTC DRUG LABEL
Date: 20110624

ACTIVE INGREDIENTS: PICEA MARIANA RESIN 10 [hp_X]/1 mL; ACONITUM NAPELLUS 200 [hp_C]/1 mL; ARSENIC TRIIODIDE 200 [hp_C]/1 mL; AVENA SATIVA FLOWERING TOP 1 [hp_X]/1 mL; STRYCHNOS IGNATII SEED 200 [hp_C]/1 mL; SUS SCROFA LUNG 6 [hp_X]/1 mL; STRYCHNOS NUX-VOMICA SEED 10 [hp_X]/1 mL; PLANTAGO MAJOR 3 [hp_X]/1 mL; QUEBRACHO BARK 3 [hp_X]/1 mL; LOBARIA PULMONARIA 200 [hp_C]/1 mL; TOBACCO LEAF 200 [hp_C]/1 mL
INACTIVE INGREDIENTS: WATER; ALCOHOL

Miracet

ACTIVE INGREDIENT

ACTIVE INGREDIENTS: Abies nigra 10X, Aconitum napellus 200C, Arsenicum iodatum 200C, Avena sativa 1X, Ignatia amara 200C, Lung suis 6X, Nux vomica 10X, Plantago major 3X, Quebracho 3X, Sticta Pulmonaria 200C, Tabacum 200C.

PURPOSE

INDICATIONS: Relieves symptoms associated with nicotine withdrawal, such as: craving for cigarettes, nervousness, insomnia, cough and increased appetite.

WARNINGS

WARNINGS: If you are pregnant or breast feeding, seek the advice of a doctor before use.

Keep out of reach of children. In case of overdose, get medical help or contact a Poison Control Center right away.

Do not use if tamper evident seal around neck of bottle is missing or broken.

DOSAGE AND ADMINISTRATION

DIRECTIONS: Adults and Children over 12: Spray twice under the tongue 3 times per day.

For children under 12: Consult a doctor prior to use.

INACTIVE INGREDIENTS: Alcohol 20% v/v, Purified water.

KEEP OUT OF REACH OF CHILDREN. In case of overdose, get medical help or contact a Poison Control Center right away.

INDICATIONS AND USAGE

INDICATIONS: Relieves symptoms associated with nicotine withdrawal, such as: craving for cigarettes, nervousness, insomnia, cough, and increased appetite.

QUESTIONS

Distributed By:

Nutralogy

2049 North Lincoln Street

Burbank, CA 91504

Made in the USA

PACKAGE LABEL

MIRACET

Nicotine Craving Relief

HOMEOPATHIC

1.0 fl. oz (30 ml)